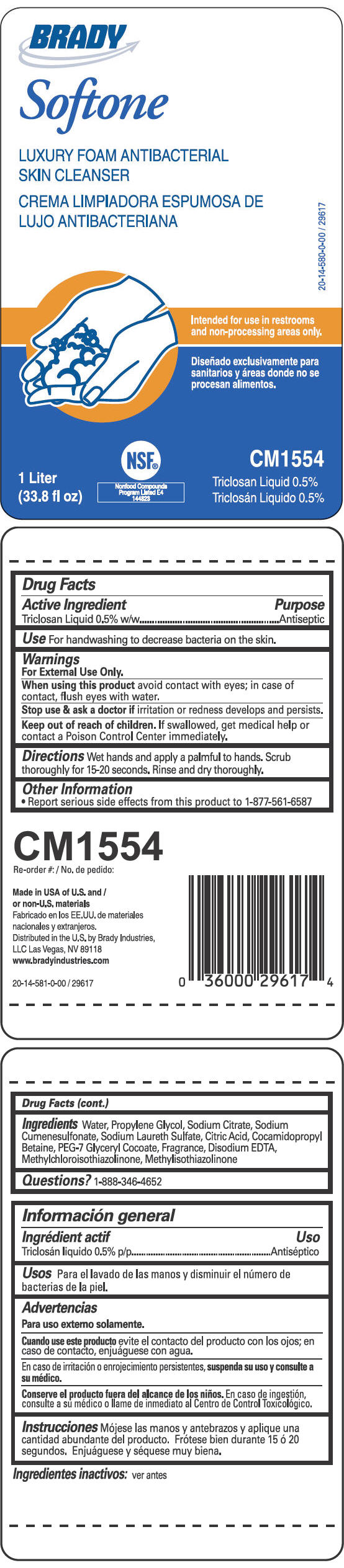 DRUG LABEL: Softone Luxury Foam Antibacterial Skin Cleanser
NDC: 76279-420 | Form: SOLUTION
Manufacturer: Brady Industries LLC
Category: otc | Type: HUMAN OTC DRUG LABEL
Date: 20110926

ACTIVE INGREDIENTS: Triclosan 5 g/1 L
INACTIVE INGREDIENTS: Water; Propylene Glycol; Sodium Citrate; Sodium Cumenesulfonate; Sodium Laureth Sulfate; Citric Acid Monohydrate; Cocamidopropyl Betaine; PEG-7 Glyceryl Cocoate; Edetate Disodium; Methylchloroisothiazolinone; Methylisothiazolinone

Softone
LUXURY FOAM ANTIBACTERIAL
SKIN CLEANSER

Drug Facts

Active Ingredient

Triclosan Liquid 0.5% w/w

Purpose

Antiseptic

Use

For handwashing to decrease bacteria on the skin.

Warnings

For External Use Only.

When using this product avoid contact with eyes; in case of contact, flush eyes with water.

Stop use & ask a doctor if irritation or redness develops and persists.

Keep out of reach of children. If swallowed, get medical help or contact a Poison Control Center immediately.

Directions

Wet hands and apply a palmful to hands. Scrub thoroughly for 15-20 seconds. Rinse and dry thoroughly.

Other Information

- Report serious side effects from this product to 1-877-561-6587

Ingredients

Water, Propylene Glycol, Sodium Citrate, Sodium Cumenesulfonate, Sodium Laureth Sulfate, Citric Acid, Cocamidopropyl Betaine, PEG-7 Glyceryl Cocoate, Fragrance, Disodium EDTA, Methylchloroisothiazolinone, Methylisothiazolinone

Questions?

1-888-346-4652

Distributed in the U.S. by Brady Industries,
LLC Las Vegas, NV 89118

PRINCIPAL DISPLAY PANEL - 1 Liter Container Label

BRADY

Softone

LUXURY FOAM ANTIBACTERIAL
SKIN CLEANSER

Intended for use in restrooms
and non-processing areas only.

1 Liter
(33.8 fl oz)

NSF®

Nonfood Compounds
Program Listed E4
144823

CM1554

Triclosan Liquid 0.5%

20-14-580-0-00 / 29617